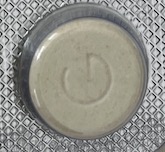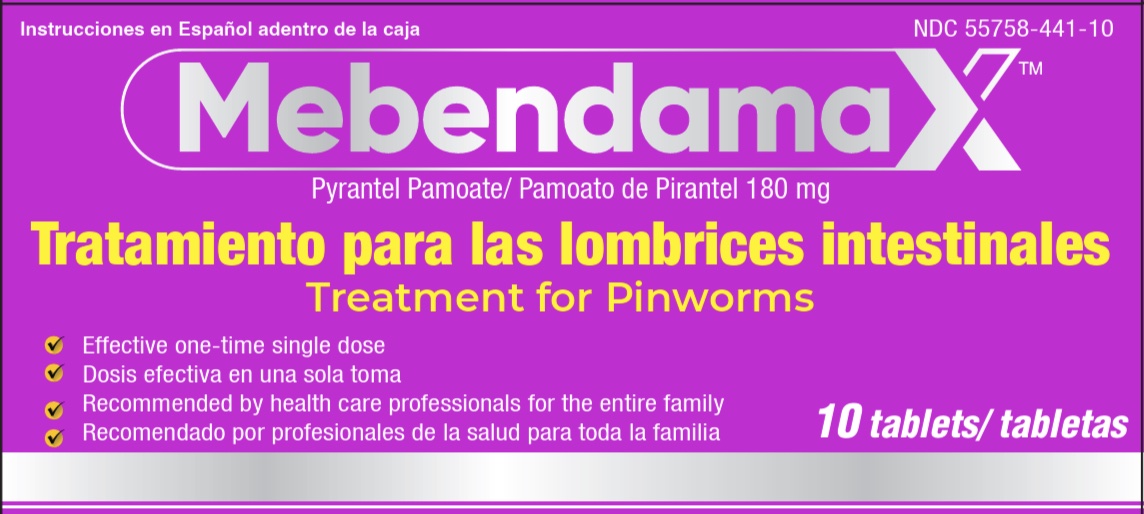 DRUG LABEL: MebendamaX
NDC: 55758-441 | Form: TABLET
Manufacturer: Pharmadel LLC
Category: otc | Type: HUMAN OTC DRUG LABEL
Date: 20250618

ACTIVE INGREDIENTS: PYRANTEL PAMOATE 180 mg/1 1
INACTIVE INGREDIENTS: CROSCARMELLOSE SODIUM; SILICON DIOXIDE; CROSPOVIDONE; LACTOSE MONOHYDRATE; MAGNESIUM STEARATE; MICROCRYSTALLINE CELLULOSE; POLYETHYLENE GLYCOL, UNSPECIFIED; POTASSIUM SORBATE; TALC; POVIDONE K30

Mebendamax Pinworm (AS)

Active ingredient & Purpose

Active ingredient (in each tablet) | Purpose
Pyrantel pamoate 180 (equivalent to 62.5mg of pyrantel base)......... | Pinworm treatment

Use

For the treatment of pinworms.

Warnings

Ask a doctor before use if you

- have liver disease
- are pregnant

Stop use and ask a doctor if

- any symptoms or pinworms are still present after treatment
- any worms other than pinworms are present before or after treatment
- any of these symptoms that sometimes occur after taking the product persist:
- abdominal cramps
- nausea
- vomiting
- diarrhea
- headache
- dizziness

Keep out of reach of children.

In case of an accidental overdose get medical help or contact a Poison Control Center right away.

Directions

READ THE PACKAGE CAREFULLY BEFORE TAKING THIS MEDICATION.

- take only according to directions
- do not exceed the recommended dosage, unless directed by a doctor
- medication should only be taken one time as a single dose; do not repeat treatment
- when one individual in a household has pinworms, the entire household should be treated unless otherwise advised
- adults, children 12 years of age and over, and children 2 years to under 12 years of age:
- this product can be taken any time of day, with or without meals. It may be taken alone or with milk or fruit juice.
- use of a laxative is not necessary before, during, or after medication
- oral dosage is a single dose of 5 mg of pyrantel base per pound or 11 mg of pyrantel base per kilogram of body weight not to exceed 1 gram (1000mg)
- children under 25 lbs. or 2yrs old: do not use unless directed by a doctor

Weight | Dosage (taken as a single (1) dose as per weight)
Less than 25 lb. or under 2 yrs. old | do not use unless directed by a doctor
25-37 lbs. | 2 tablets (125 mg)
38-62 lbs. | 4 tablets (250 mg)
63-87 lbs. | 6 tablets (375 mg)
88-112 lbs. | 8 tablets (500 mg)
113-137 lbs. | 10 tablets (625 mg)
138-162 lbs. | 12 tablets (750 mg)
163-187 lbs. | 14 tablets (875 mg)
188 lbs. and over | 16 tablets (1,000 mg)

Inactive ingredients

croscarmellose sodium, crospovidone, lactose monohydrate, magnesium stearate, microcrystalline cellulose, polyethylene glycol, potassium sorbate, povidone k-30, silicon dioxide, talc

Dist. by:

Pharmadel LLC.

New Castle, DE 19720

1-866-359-3478